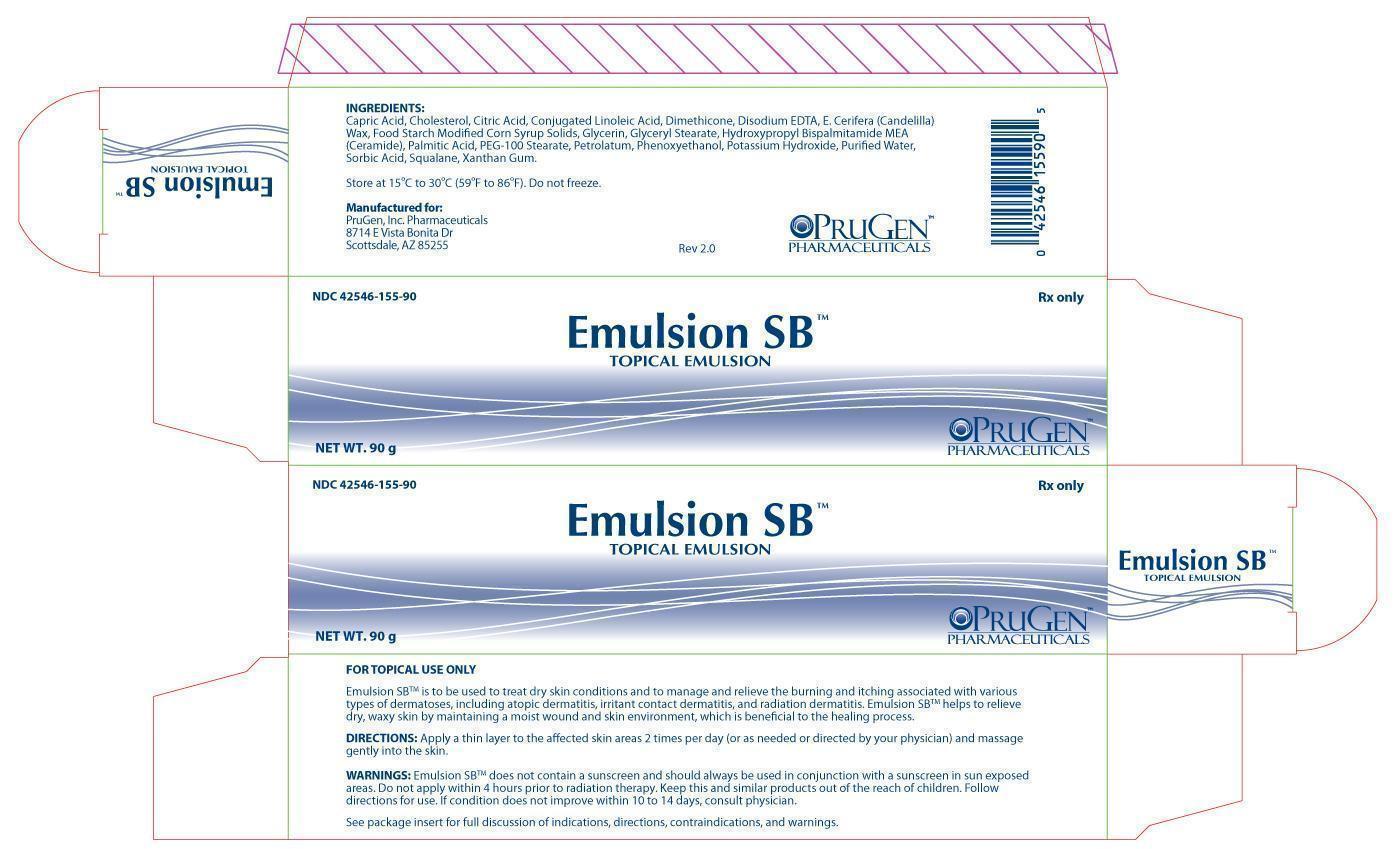 DRUG LABEL: Emulsion SB
NDC: 42546-155
Manufacturer: PruGen, Inc.
Category: other | Type: PRESCRIPTION MEDICAL DEVICE LABEL
Date: 20120829

Emulsion SB External Emulsion

DESCRIPTION

Emulsion SB is a steroid-free, fragrance-free, ceramide formulation.

INDICATIONS & USAGE

Emulsion SB is to be used to treat dry skin conditions and to manage and relieve the burning and itching associated with various types of dermatoses, including atopic dermatitis, irritant contact dermatitis, and radiation dermatitis. Emulsion SB helps to relieve dry, waxy skin by maintaining a moist wound and skin environment, which is beneficial to the healing process.

CONTRAINDICATIONS

Emulsion SB is contraindicated in persons with known hypersensitivity to any of the components of the formulation.

WARNINGS

• Emulsion SB does not contain a sunscreen and should always be used in conjunction with a sunscreen in sun exposed areas

• Do not apply within 4 hours prior to radiation therapy

• Keep this and similar products out of the reach of children

• Follow directions for use

• If condition does not improve within 10 to 14 days, consult physician

PRECAUTIONS AND OBSERVATIONS

For the treatment of any dermal wound, consult a physician.

• Use Emulsion SB only as directed

• Emulsion SB is for external use only and should not be ingested or taken internally

• If clinical signs of infection are present, appropriate treatment should be initiated. If clinically indicated, use of Emulsion SB may be continued during the anti-infective therapy

• In radiation dermatitis and/or in conjunction with ongoing radiation therapy, apply following radiation therapy or as indicated by the radiation therapist

INSTRUCTIONS FOR USE

Apply a thin layer to the affected skin areas 2 times per day (or as needed or directed by your physician) and massage gently into the skin. If the skin is broken, cover Emulsion SB with a dressing of choice.

INGREDIENTS

Capric Acid, Cholesterol, Citric Acid, Conjugated Linoleic Acid, Dimethicone, Disodium EDTA, E. Cerifera (Candelilla) Wax, Food Starch Modified Corn Syrup Solids, Glycerin, Glyceryl Stearate, Hydroxypropyl Bispalmitamide MEA (Ceramide), Palmitic Acid, PEG-100 Stearate, Petrolatum, Phenoxyethanol, Potassium Hydroxide, Purified Water, Sorbic Acid, Squalane, Xanthan Gum.

HOW SUPPLIED

Emulsion SB is supplied as follows:

NDC 42546-155-90: 90 gram tube

NDC 42546-155-50: 50 gram tube

NDC 42546-155-52: Package contains two 50 gram tubes

Store at 15ºC to 30ºC (59ºF to 86ºF). Do not freeze.

Rx ONLY - Prescription Medical Device; Federal Law restricts this device to sale by or on the order of a physician.

Manufactured for:

PruGen, Inc. Pharmaceuticals

8714 E Vista Bonita Dr

Scottsdale, AZ 85255

Emulsion SB Carton Label

NDC 42546-155-90

Emulsion SB Topical Emulsion

Rx Only

90g

PruGen, Inc. Pharmaceuticals